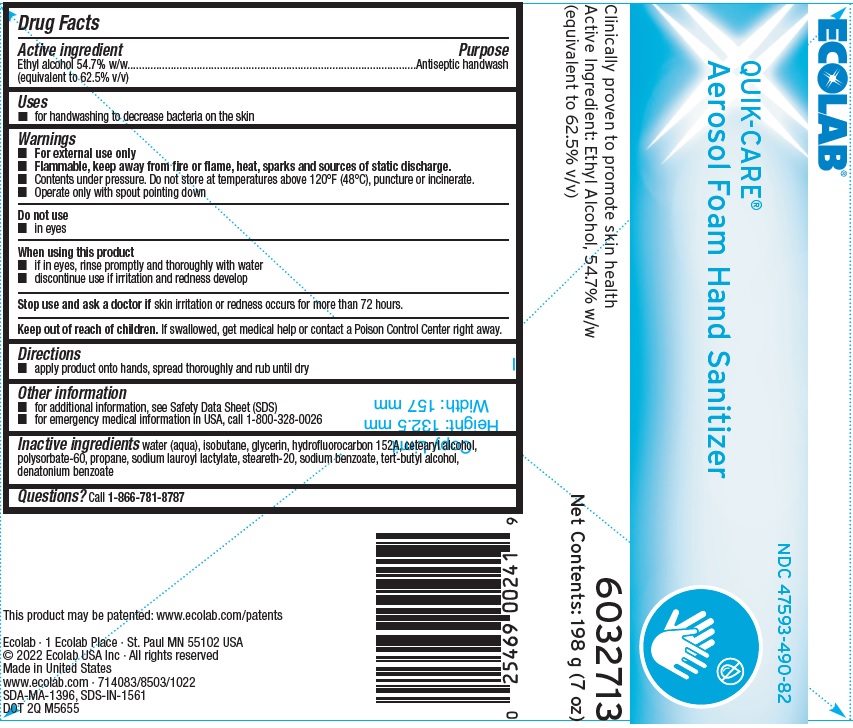 DRUG LABEL: Quik-Care
NDC: 47593-490 | Form: SOLUTION
Manufacturer: Ecolab Inc.
Category: otc | Type: HUMAN OTC DRUG LABEL
Date: 20240404

ACTIVE INGREDIENTS: ALCOHOL 54.7 g/100 g
INACTIVE INGREDIENTS: Water; isobutane; GLYCERIN; 1,1-DIFLUOROETHANE; CETOSTEARYL ALCOHOL; POLYSORBATE 60; PROPANE; SODIUM LAUROYL LACTYLATE; STEARETH-20; SODIUM BENZOATE; TERT-BUTYL ALCOHOL; DENATONIUM BENZOATE

Drug Facts

Active Ingredient

Ethyl alcohol 54.7 w/w (equivalent to 62.5% v/v)

Purpose

Antiseptic Handwash

Uses

- For handwashing to decrease bacteria on the skin

Warnings

- For external use only
- Flammable, keep away from fire or flame, heat, sparks and sources of static discharge.
- Contents under pressure. Do not store at temperatures above 120°F (48°C), puncture or incinerate
- Operate only with spout pointing down

Do not use

- In eyes

When using this product

- If in eyes, rinse promptly and thoroughly with water
- Discontinue use if irritation and redness develop

Stop use and ask a doctor if skin irritation or redness develop occurs for more than 72 hours

Keep out of reach of children. If swallowed, get medical help or contact a Poison Control Center right away

Directions

- Apply product onto hands, spread thoroughly and rub until dry

Other Information

- for additional information, see Safety Data Sheet (SDS)
- for emergency medical informatnio in the USA, call 1-800-328-0026

INACTIVE INGREDIENT

Inactive Ingredients water (aqua), isobutane, glycerin, hydrofluorocarbon 152A, cetearyl alcohol, polysorbate-60, propane, sodium lauroyl lactylate, steareth-20, sodium benzoate, tert-butyl alcohol, denatonium benzoate

Questions? Call 1-866-781-8787

Representative Label and Principal Display Panel

ECOLAB®

47593-490-82

QUIK-CARE Aerosol Foam Hand Sanitizer

Clinically proven to promote skin health

Active Ingredient: 57.4% w/w (equivalent to 62.5% v/v)

6032713

Net Contents: 198 g (7 oz)

Ecolab · 1 Ecolab Place · St. Paul MN 55102 USA

© 2022 Ecolab USA Inc · All rights reserved

Made in United States

www.ecolab.com · 714083/8503/1022

SDA-MA-1396, SDS-IN-1561

DOT 2Q M5655